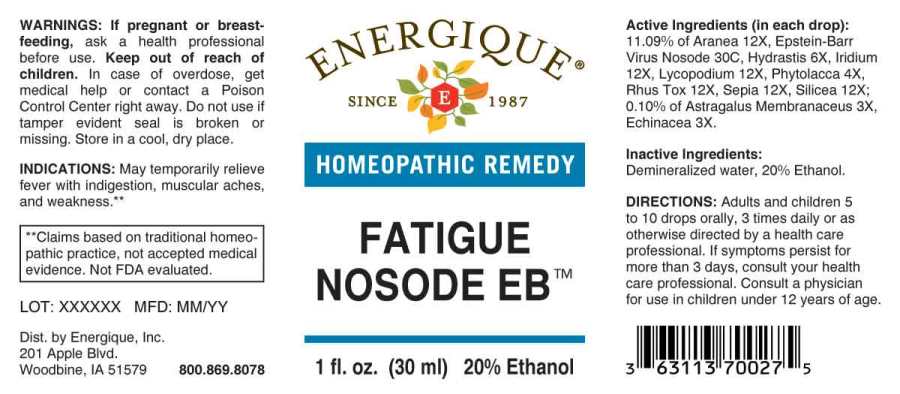 DRUG LABEL: FATIGUE NOSODE EB
NDC: 44911-0608 | Form: LIQUID
Manufacturer: Energique, Inc.
Category: homeopathic | Type: HUMAN OTC DRUG LABEL
Date: 20241024

ACTIVE INGREDIENTS: ASTRAGALUS PROPINQUUS ROOT 3 [hp_X]/1 mL; ECHINACEA ANGUSTIFOLIA WHOLE 3 [hp_X]/1 mL; PHYTOLACCA AMERICANA ROOT 4 [hp_X]/1 mL; GOLDENSEAL 6 [hp_X]/1 mL; ARANEUS DIADEMATUS 12 [hp_X]/1 mL; IRIDIUM 12 [hp_X]/1 mL; LYCOPODIUM CLAVATUM SPORE 12 [hp_X]/1 mL; TOXICODENDRON PUBESCENS LEAF 12 [hp_X]/1 mL; SILICON DIOXIDE 12 [hp_X]/1 mL; SEPIA OFFICINALIS JUICE 12 [hp_X]/1 mL; HUMAN HERPESVIRUS 4 30 [hp_C]/1 mL
INACTIVE INGREDIENTS: WATER; ALCOHOL

DRUG FACTS:

ACTIVE INGREDIENTS:

(in each drop): 11.09% of Aranea Diadema 12X, Epstein-Barr Virus Nosode 30X, Hydrastis Canadensis 6X, Iridium Metallicum 12X, Lycopodium Clavatum 12X, Phytolacca Decandra 4X, Rhus Tox 12X, Sepia 12X Silicea 12X; 0.10% of Astragalus Membranaceus 3X, Echinacea (Angustifolia) 3X.

INDICATIONS:

May temporarily relieve fever with indigestion, muscular aches and weakness.**

**Claims based on traditional homeopathic practice, not accepted medical evidence. Not FDA evaluated.

WARNINGS:

If pregnant or breast-feeding, ask a health professional before use.

Keep out of reach of children. In case of overdose, get medical help or contact a Poison Control Center right away.

Do not use if tamper evident seal is broken or missing. Store in a cool, dry place.

Keep out of reach of children. In case of overdose, get medical help or contact a Poison Control Center right away.

DIRECTIONS:

Adults and children 5 to 10 drops orally, 3 times daily or as otherwise directed by a health care professional. If symptoms persist for more than 3 days, consult your health care professional. Consult a physician for use in children under 12 years of age.

INDICATIONS:

May temporarily relieve fever with indigestion, muscular aches and weakness.**

**Claims based on traditional homeopathic practice, not accepted medical evidence. Not FDA evaluated.

INACTIVE INGREDIENTS:

Demineralized water, 20% Ethanol

QUESTIONS:

Dist. by Energique, Inc.

201 Apple Blvd

Woodbine, IA 51579 800.869.8078

PACKAGE LABEL DISPLAY:

ENERGIQUE
SINCE 1987
HOMEOPATHIC REMEDY
FATIGUE NOSODE EB
1 fl. oz. (30 ml)